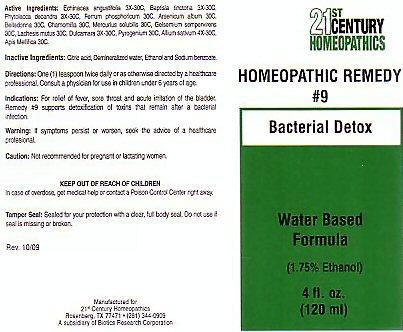 DRUG LABEL: CENTURY 21 BACTERIAL DETOX
NDC: 63972-009 | Form: LIQUID
Manufacturer: 21st Century Homeopathics, Inc
Category: homeopathic | Type: HUMAN OTC DRUG LABEL
Date: 20100101

ACTIVE INGREDIENTS: ECHINACEA ANGUSTIFOLIA 30 [hp_C]/5 mL; BAPTISIA TINCTORIA ROOT 30 [hp_C]/5 mL; PHYTOLACCA AMERICANA ROOT 30 [hp_C]/5 mL; FERROSOFERRIC PHOSPHATE 30 [hp_C]/5 mL; ARSENIC TRIOXIDE 30 [hp_C]/5 mL; ATROPA BELLADONNA 30 [hp_C]/5 mL; MATRICARIA RECUTITA 30 [hp_C]/5 mL; MERCURIUS SOLUBILIS 30 [hp_C]/5 mL; GELSEMIUM SEMPERVIRENS ROOT 30 [hp_C]/5 mL; LACHESIS MUTA VENOM 30 [hp_C]/5 mL; SOLANUM DULCAMARA TOP 30 [hp_C]/5 mL; RANCID BEEF 30 [hp_C]/5 mL; GARLIC 30 [hp_C]/5 mL; APIS MELLIFERA 30 [hp_C]/5 mL
INACTIVE INGREDIENTS: CITRIC ACID MONOHYDRATE; WATER; ALCOHOL; SODIUM BENZOATE

Active Ingredients

Active Ingredients: Echinacea angustifolia 3X-30C, Baptisia tinctoria 3X-30C, Phytolacca decandra 3X-30C, Ferrum phosphoricum 30C, Arsenicum album 30C, Belladonna 30C, Charmomilla 30C, Mercurius solubilis 30C, Gelsemium sempervirens 30C, Lachesis mutus 30C, Dulcamara 3X-30C, Pyrogenium 30C, Allium sativum 4X-30C, Apis Mellifica 30C.

Inactive Ingredients

Inactive Ingredients: Citric acid, demineralized water, Ethanol and Sodium benzoate.

Directions For Use

Directions: One (1) teaspoon twice daily or as directed by a healthcare professional. Consult a physician for use in children under 6 years of age

Indications

Indications: For relief of fever, sore throat and acute irritation of the bladder. Remedy # 9 supports detoxification of toxins that remain after a bacterial infection.

Keep Out Of Reach Of Children

In case of overdose, get medical help or contact a Poison Control Center right away.

Purpose

Bacterial Detox

Warnings

Warning: If symptoms persist or worsen, seek the advice of a healthcare professional.
Caution: Not recommended for pregnant or lactating women.

Product Label

21st CENTURY HOMEOPATHICS
HOMEOPATHIC REMEDY #9 Bacterial Detox
Water Based Formula (1.75% Ethanol) 4 fl. oz. (120ml)
Tamper Seal: Sealed for your protection with a clear, full body seal. Do not use if seal is missing or broken.
Rev. 10/09 Manufactured for 21st Century Homeopathics Rosenburg, Tx 77471 (281) 344-0909 A subsidiary of Biotics Research Corporation